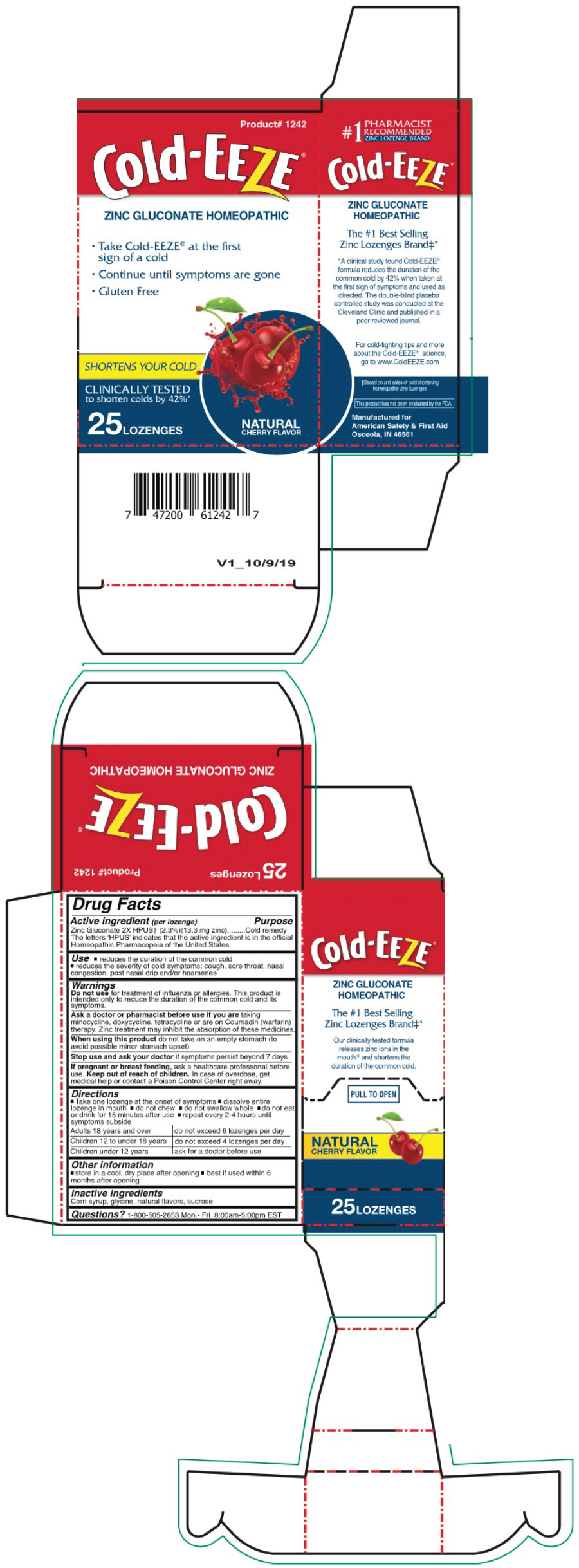 DRUG LABEL: COLD EEZE
NDC: 73598-1242 | Form: LOZENGE
Manufacturer: JHK Inc dba American Safety & First Aid
Category: homeopathic | Type: HUMAN OTC DRUG LABEL
Date: 20251216

ACTIVE INGREDIENTS: ZINC GLUCONATE 2 [hp_X]/1 1
INACTIVE INGREDIENTS: CORN SYRUP; GLYCINE; SUCROSE

Cold Eeze®

Drug Facts

Active Ingredient (per lozenge)

Zinc Gluconate 2X HPUS (2.3%) (13.3mg Zinc)

The letters 'HPUS' indicate that the active ingredient is in the official Homeopathic Pharmacopoeia of the United States.

Purpose

Cold Remedy

Uses

- Reduces the duration of the common cold
- Reduces the severity of cold symptoms: cough, sore throat, nasal congestion, post nasal drip and/or hoarseness

Warnings

Do not use for treatment of influenza or allergies. The product is only intended to reduce the duration of the common cold and its symptoms.

Ask a doctor or pharmacist before use if you are taking minocycline, doxycycline, tetracycline or are on coumadin therapy. Zinc treatment may inhibit the absorption of these medicines.

When using this product do not take on an empty stomach (to avoid possible minor stomach upset).

Stop use and ask your doctor if symptoms persist beyond 7 days.

PREGNANCY OR BREAST FEEDING

If pregnant or breastfeeding, ask a health professional before use.

Keep out of reach of children. In case of overdose, get medical help or contact a Poison Control Center right away.

Directions

- Take one lozenge at the onset of symptoms
- Dissolve the entire lozenge in the mouth
- Do not chew
- Do not swallow whole
- Do not eat or drink for 15 minutes after use
- Repeat every 2-4 hours until symptoms subside.

Adults 18 years and over - do not exceed 6 lozenges per day
Children 12 - 18 years - do not exceed 4 lozenges per day
Children under 12 years - ask a doctor before use

Other Information

- Store in a cool, dry place after opening
- Best if used within 6 months after opening

Inactive Ingredients

Corn syrup, glycine, natural flavors and sucrose

Questions?

1-800-505-2653 Mon.- Fri. 8:00am-5:00pm EST

PRINCIPAL DISPLAY PANEL - 25 Lozenge Box

Product# 1242

Cold-EEZE®

ZINC GLUCONATE HOMEOPATHIC

- Take Cold-EEZE® at the first
  sign of a cold
- Continue until symptoms are gone
- Gluten Free

SHORTENS YOUR COLD

CLINICALLY TESTED
to shorten colds by 42%*

25 LOZENGES

NATURAL
CHERRY FLAVOR